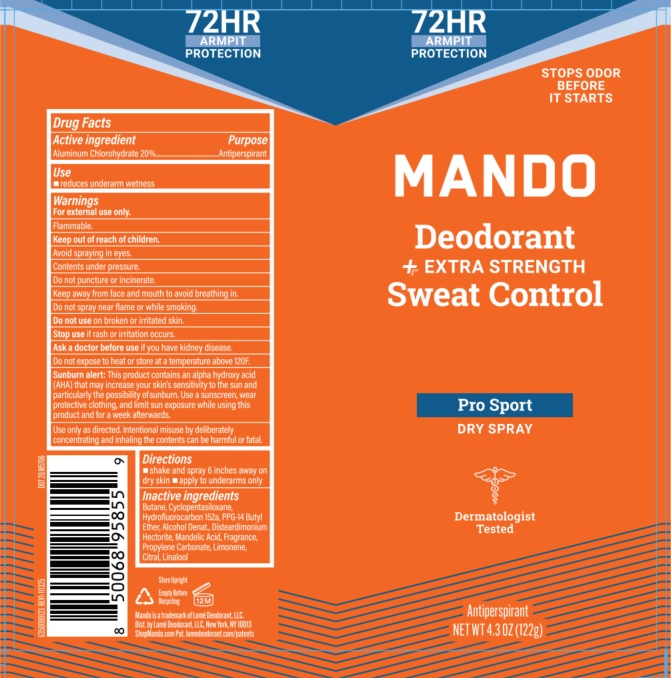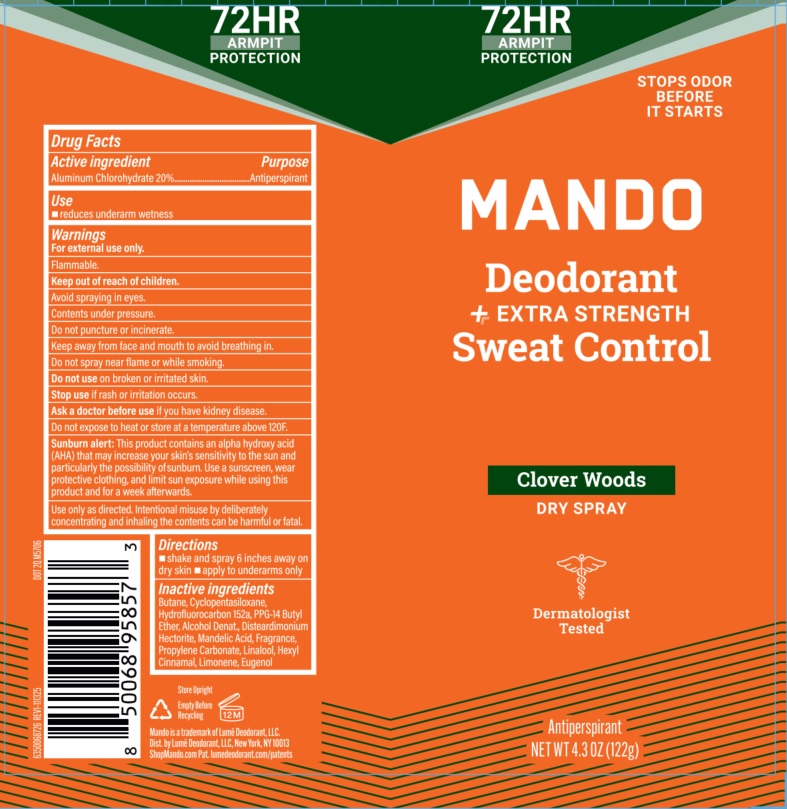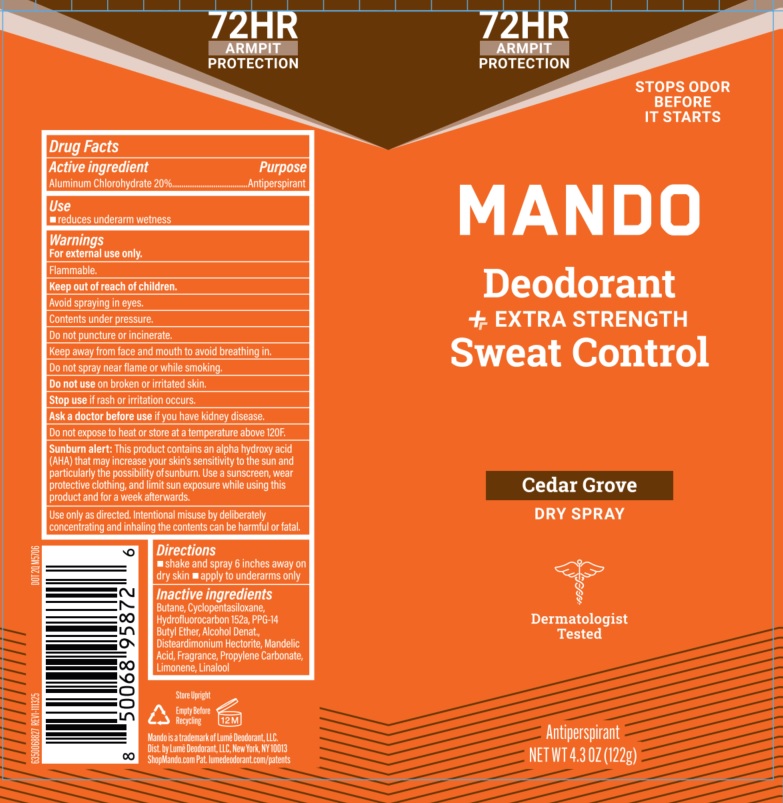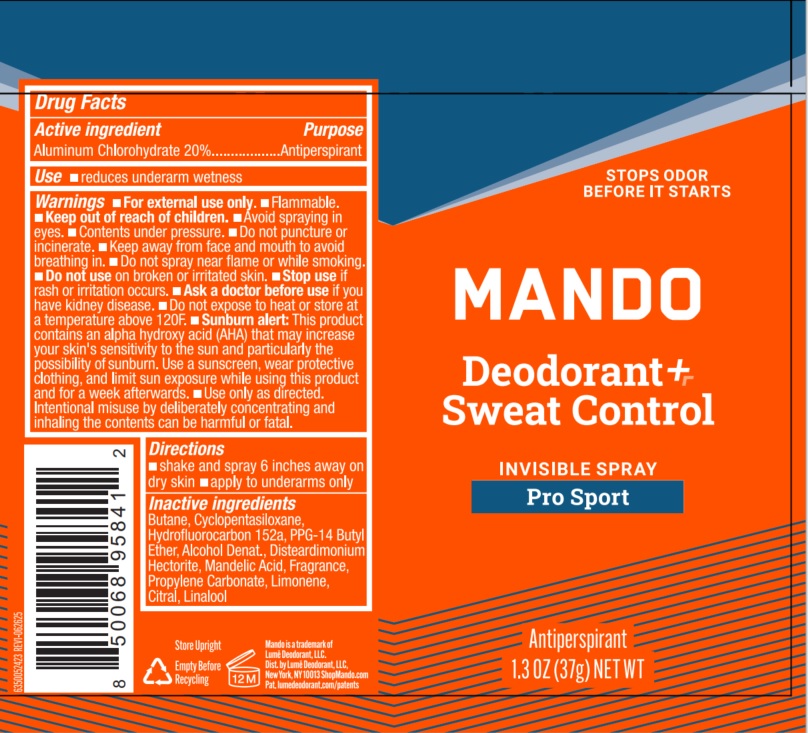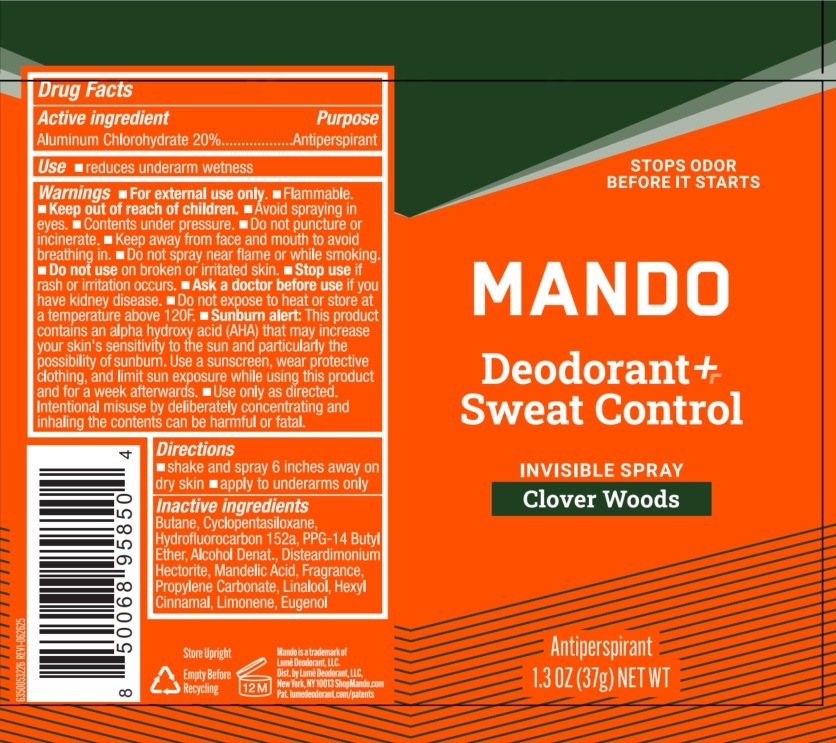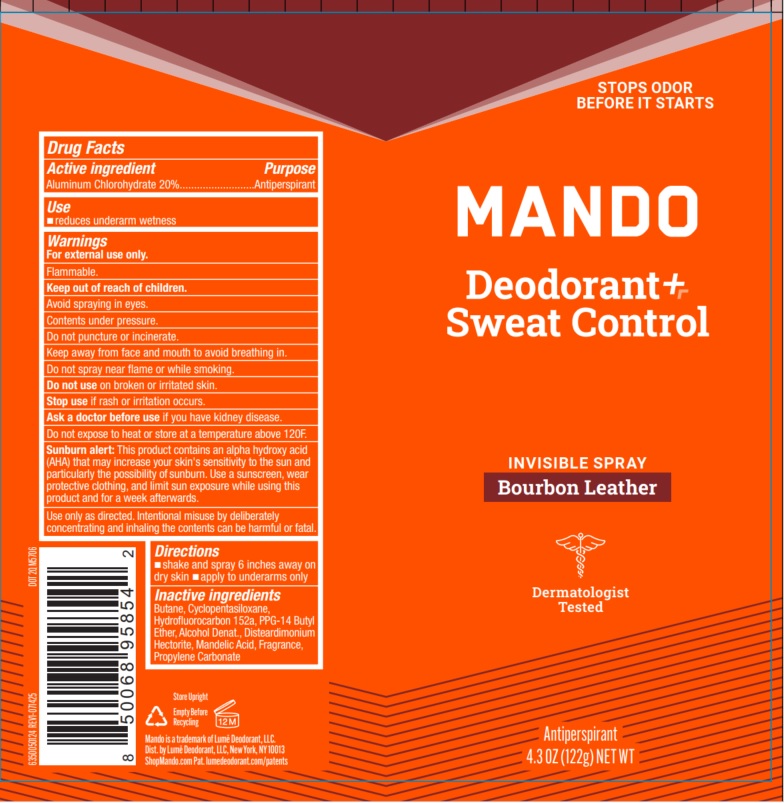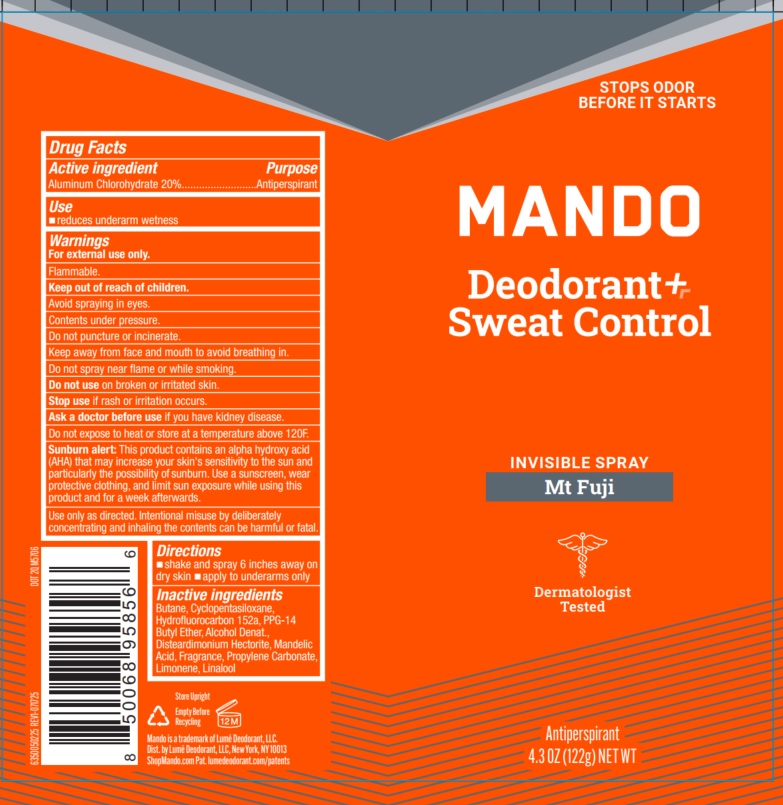 DRUG LABEL: Mando

NDC: 84520-025 | Form: AEROSOL, SPRAY
Manufacturer: Lume Deodorant, LLC.
Category: otc | Type: HUMAN OTC DRUG LABEL
Date: 20260209

ACTIVE INGREDIENTS: ALUMINUM CHLOROHYDRATE 20 g/100 g
INACTIVE INGREDIENTS: BUTANE; MANDELIC ACID; DISTEARDIMONIUM HECTORITE; HYDROFLUOROCARBON 152A; PROPYLENE CARBONATE; ALCOHOL; PPG-14 BUTYL ETHER; CYCLOPENTASILOXANE

Mando

Active ingredient

Aluminum Chlorohydrate 20%

Purpose

Antiperspirant

INDICATIONS AND USAGE

Use• reduces underarm wetness

Warnings

For external use only

• Flammable • Avoid spraying in eyes • Contents under pressure. • Do not puncture or incinerate. • Keep away from face and mouth to avoid breathing in. • Do not spray near flame or while smoking. • Do not expose to heat or store at a temperature above 120F.

Sunburn alert:This product contains an alpha hydroxy acid (AHA) that may increase your skin's sensitivity to the sun and particularly the possibility of sunburn. Use a sunscreen, wear protective clothing, and limit sun exposure while using this product and for a week afterwards. • Use only as directed.

Intentional misuse by deliberately concentrating and inhaling the contents can be harmful or fatal.

Do not useon broken or irritated skin

Stop useif rash or irritation occurs.

Ask a doctor before useif you have kidney disease

Keep out of reach of children.

Directions

• shake and spray 6 inches away on dry skin • apply to underarms only

Pro Sport Dry Spray

Inactive ingredients

Butane, Cyclopentasiloxane, Hydrofluorocarbon 152a, PPG-14 Butyl Ether, Alcohol Denat., Disteardimonium Hectorite, Mandelic Acid, Fragrance,Propylene Carbonate, Limonene, Citral, Linalool

Clover Woods Dry Spray

Inactive ingredients

Butane, Cyclopentasiloxane, Hydrofluorocarbon 152a, PPG-14 Butyl Ether, Alcohol Denat., Disteardimonium Hectorite, Mandelic Acid, Fragrance, Propylene Carbonate, Linalool, Hexyl Cinnamal, Limonene, Eugenol

Cedar Grove Dry Spray

Inactive ingredients

Butane, Cyclopentasiloxane, Hydrofluorocarbon 152a, PPG-14 Butyl Ether, Alcohol Denat., Disteardimonium Hectorite, Mandelic Acid, Fragrance, Propylene Carbonate, Limonene, Linalool

Pro Sport Invisible Spray

Inactive ingredients

Butane, Cyclopentasiloxane, Hydrofluorocarbon 152a, PPG-14 Butyl Ether, Alcohol Denat., Disteardimonium Hectorite, Mandelic Acid, Fragrance, Propylene Carbonate, Limonene, Citral, Linalool

Clover Woods Invisible Spray

Inactive ingredients

Butane, Cyclopentasiloxane, Hydrofluorocarbon 152a, PPG-14 Butyl Ether, Alcohol Denat., Disteardimonium Hectorite, Mandelic Acid, Fragrance, Propylene Carbonate, Linalool, Hexyl Cinnamal, Limonene, Eugenol

Bourbon Leather Invisible Spray

Inactive ingredients

Butane, Cyclopentasiloxane, Hydrofluorocarbon 152a, PPG-14 Butyl Ether, Alcohol Denat., Disteardimonium Hectorite, Mandelic Acid, Fragrance, Propylene Carbonate

Mt Fuji Invisible Spray

Inactive ingredients

Butane, Cyclopentasiloxane, Hydrofluorocarbon 152a, PPG-14 Butyl Ether, Alcohol Denat., Disteardimonium Hectorite, Mandelic Acid, Fragrance, Propylene Carbonate, Limonene, Linalool

Dry Spray

72 HR ARMPIT PROTECTION

STOPS ODOR BEFORE IT STARTS

MANDO

Deodorant + EXTRA STRENGTH Sweat Control

Antiperspirant

NET WT 4.3 OZ (122g)

Store Upright

Empty Before Recycling

Mando is a trademark of Lume Deodorant, LLC.

Dist. by Lume Deodorant, LLC, New York, NY 10013

ShopMando.com Pat. lumedeodorant.com/patents

Invisible Spray

STOPS ODOR BEFORE IT STARTS

MANDO

Deodorant + Sweat Control

Antiperspirant

1.3 OZ (37g) NET WT

Store Upright

Empty Before Recycling

Mando is a trademark of Lume Deodorant, LLC.

Dist. by Lume Deodorant, LLC, New York, NY 10013

ShopMando.com Pat. lumedeodorant.com/patents